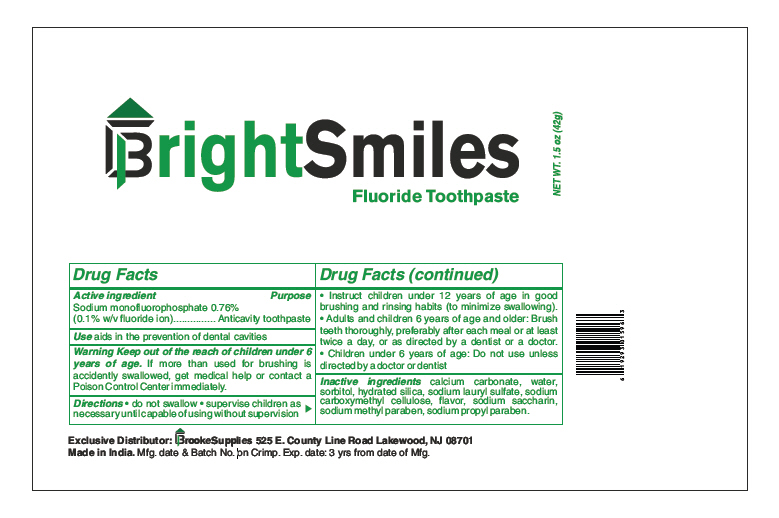 DRUG LABEL: Bright Smiles
NDC: 71074-108 | Form: PASTE, DENTIFRICE
Manufacturer: Brooke Supplies
Category: otc | Type: HUMAN OTC DRUG LABEL
Date: 20170127

ACTIVE INGREDIENTS: Sodium Monofluorophosphate 0.1 g/100 g
INACTIVE INGREDIENTS: CALCIUM CARBONATE; WATER; SORBITOL; HYDRATED SILICA; SODIUM LAURYL SULFATE; CARBOXYMETHYLCELLULOSE SODIUM, UNSPECIFIED FORM; SACCHARIN SODIUM; METHYLPARABEN SODIUM; PROPYLPARABEN SODIUM

Bright Smiles

Drug Facts

Active ingredient

Sodium monofluorophosphate 0.76% (0.1% w/v fluoride ion)

Purpose

Anticavity toothpaste

Use

aids in the prevention of dental cavities

Warning

KEEP OUT OF REACH OF CHILDREN

Keep out of the reach of children under 6 years of age. If more than used for brushing is accidently swallowed, get medical help or contact a Poison Control Center immediately.

Directions

- do not swallow
- supervise children as necessary until capable of using without supervision
- Instruct children under 12 years of age in good brushing and rinsing habits (to minimize swallowing).
- Adults and children 6 years of age and older: Brush teeth thoroughly, preferably after each meal or at least twice a day, or as directed by a dentist or a doctor.
- Children under 6 years of age: Do not use unless directed by a doctor or dentist

Inactive ingredients

calcium carbonate, water, sorbitol, hydrated silica, sodium lauryl sulfate, sodium carboxymethyl cellulose, flavor, sodium saccharin, sodium methyl paraben, sodium propyl paraben.

PRINCIPAL DISPLAY PANEL - 42 g Tube Label

BrightSmiles
Fluoride Toothpaste

NET WT. 1.5 oz (42g)